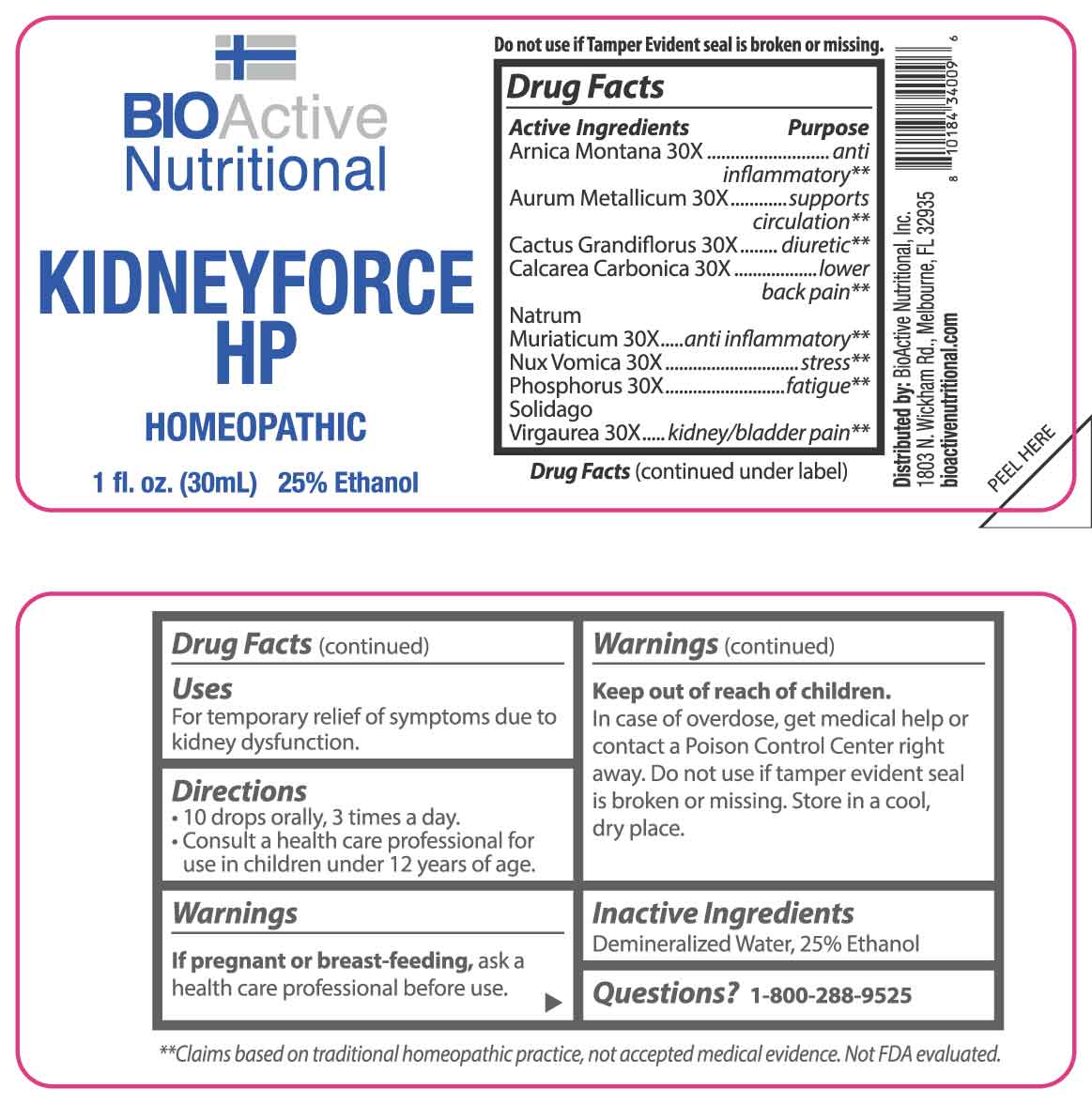 DRUG LABEL: Kidneyforce-HP
NDC: 43857-0586 | Form: LIQUID
Manufacturer: BioActive Nutritional, Inc.
Category: homeopathic | Type: HUMAN OTC DRUG LABEL
Date: 20250402

ACTIVE INGREDIENTS: ARNICA MONTANA WHOLE 30 [hp_X]/1 mL; GOLD 30 [hp_X]/1 mL; SELENICEREUS GRANDIFLORUS STEM 30 [hp_X]/1 mL; OYSTER SHELL CALCIUM CARBONATE, CRUDE 30 [hp_X]/1 mL; SODIUM CHLORIDE 30 [hp_X]/1 mL; STRYCHNOS NUX-VOMICA SEED 30 [hp_X]/1 mL; PHOSPHORUS 30 [hp_X]/1 mL; SOLIDAGO VIRGAUREA FLOWERING TOP 30 [hp_X]/1 mL
INACTIVE INGREDIENTS: WATER; ALCOHOL

DRUG FACTS:

ACTIVE INGREDIENTS:

Arnica Montana 30X, Aurum Metallicum 30X, Cactus Grandiflorus 30X, Calcarea Carbonica 30X, Natrum Muriaticum 30X, Nux Vomica 30X, Phosphorus 30X, Solidago Virgaurea 30X.

PURPOSE:

Arnica Montana – anti inflammatory,** Aurum Metallicum – supports circulation,** Cactus Grandiflorus - diuretic,** Calcarea Carbonica – lower back pain,** Natrum Muriaticum – anti inflammatory,** Nux Vomica - stress,** Phosphorus – fatigue,** Solidago Virgaurea – kidney/bladder pain.**

** Claims based on traditional homeopathic practice, not accepted medical evidence. Not FDA evaluated.

USES:

For temporary relief of symptoms due to kidney dysfunction.

WARNINGS:

If pregnant or breast-feeding, ask a health care professional before use.

Keep out of reach of children. In case of overdose, get medical help or contact a Poison Control Center right away.

Do not use if tamper evident seal is broken or missing.

Store in a cool, dry place.

KEEP OUT OF REACH OF CHILDREN:

In case of overdose, get medical help or contact a Poison Control Center right away.

DIRECTIONS:

• 10 drops orally, 3 times a day.

• Consult a health care professional for use in children under 12 years of age.

INACTIVE INGREDIENTS:

Demineralized Water, 25% Ethanol

QUESTIONS:

Distributed by:
BioActive Nutritional, Inc.
1803 N. Wickham Rd.
Melbourne, FL 32935
bioactivenutritional.com

1-800-288-9525

PACKAGE LABEL DISPLAY:

BIOActive Nutritional

KIDNEYFORCE HP

HOMEOPATHIC

1 FL OZ (30 ml)